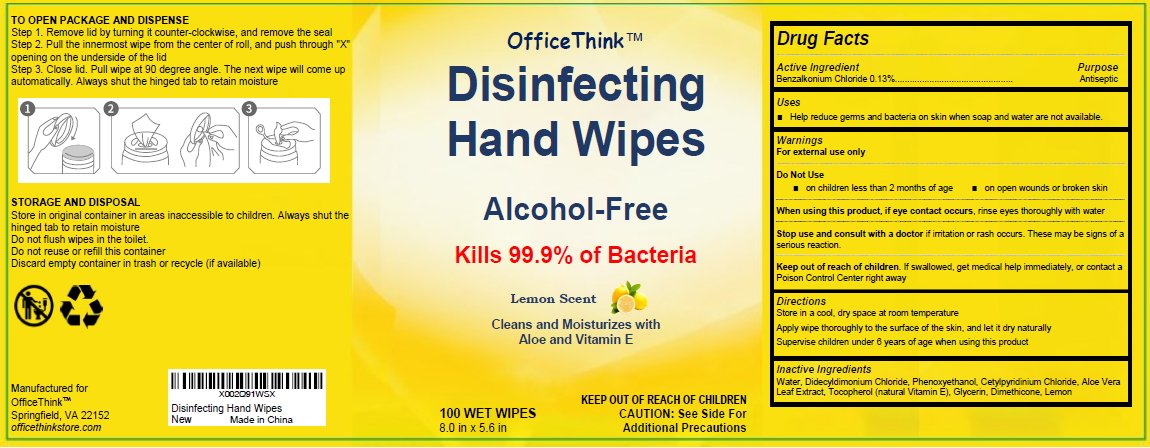 DRUG LABEL: DISINFECT Wet WIPES
NDC: 80262-701 | Form: CLOTH
Manufacturer: Aarjay Products LLC
Category: otc | Type: HUMAN OTC DRUG LABEL
Date: 20201202

ACTIVE INGREDIENTS: BENZALKONIUM CHLORIDE 0.13 1/100 1
INACTIVE INGREDIENTS: CETYLPYRIDINIUM CHLORIDE; DIMETHICONE; GLYCERIN; DIDECYLDIMONIUM CHLORIDE; WATER; TOCOPHEROL; ALOE VERA LEAF; LEMON; PHENOXYETHANOL

Disinfecting Wet Wipes

Disinfecting Wet Wipes

Active Ingredient(s)

BENZALKONIUM CHLORIDE 0.13%. Purpose: Antiseptic

Purpose

Antiseptic, Disinfecting Wet Wipes

Use

DISINFECT Wet WIPES to help reduce bacteria that potentially can cause disease. For use when soap and water are not available.

Warnings

For external use only

Do not use

- on children less than 2 months of age
- on open skin wounds or broken skin

When using this product keep out of eyes, ears, and mouth. In case of contact with eyes, rinse eyes thoroughly with water.
Stop use and ask a doctor if irritation or rash occurs. These may be signs of a serious condition.
Keep out of reach of children. If swallowed, get medical help or contact a Poison Control Center right away.

Stop use and ask a doctor if irritation or rash occurs. These may be signs of a serious condition.

Keep out of reach of children. If swallowed, get medical help or contact a Poison Control Center right away.

Directions

- Wipe the surface of the skin and let it dry naturally.
- Supervise children under 6 years of age when using this product to avoid swallowing.

Other information

- Store between 15-30C (59-86F)
- Avoid freezing and excessive heat above 40C (104F)

Inactive ingredients

WATER
DIDECYLDIMONIUM CHLORIDE
PHENOXYETHANOL
CETYLPYRIDINIUM CHLORIDE
ALOE VERA LEAF
TOCOPHEROL
GLYCERIN
DIMETHICONE
LEMON